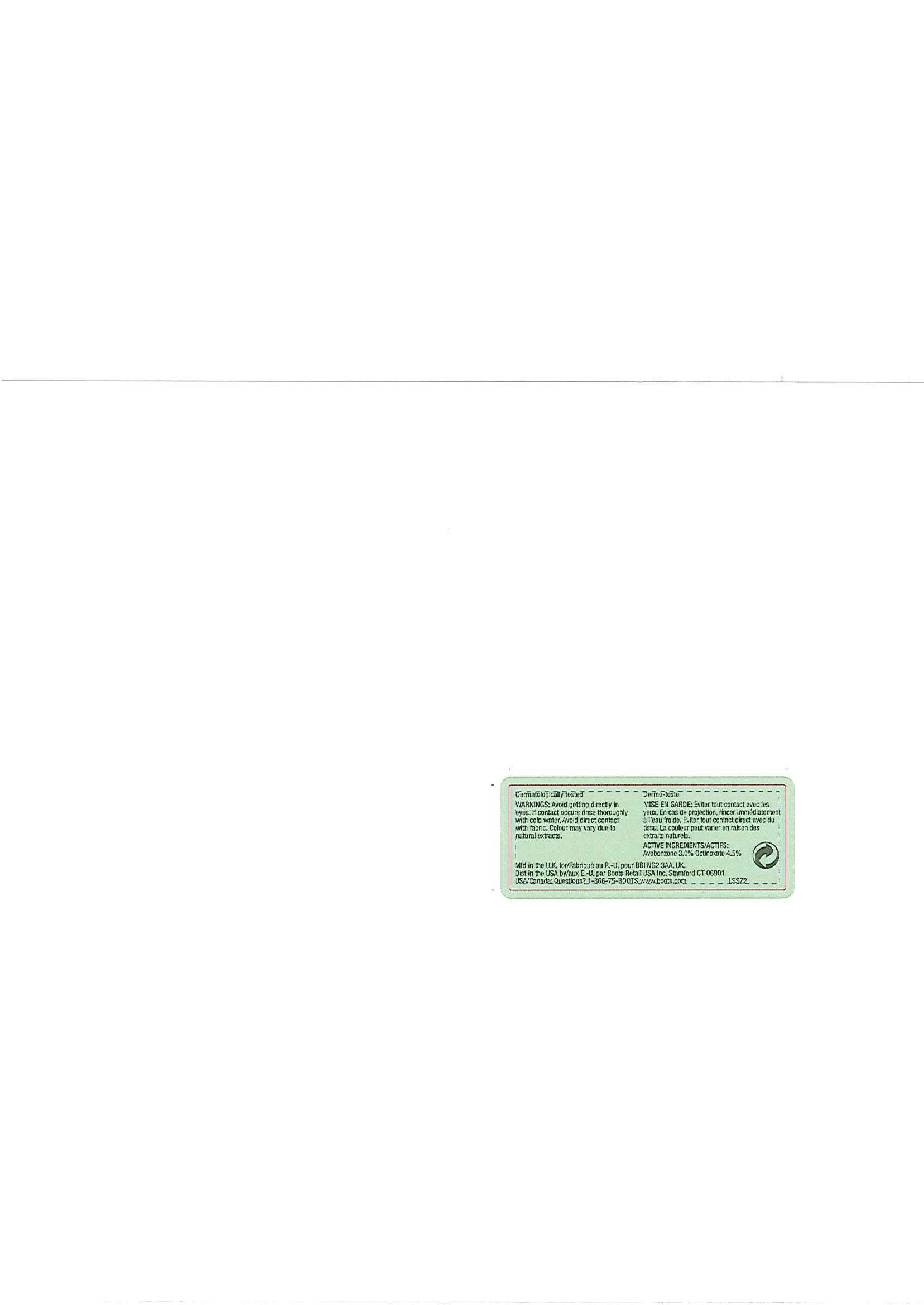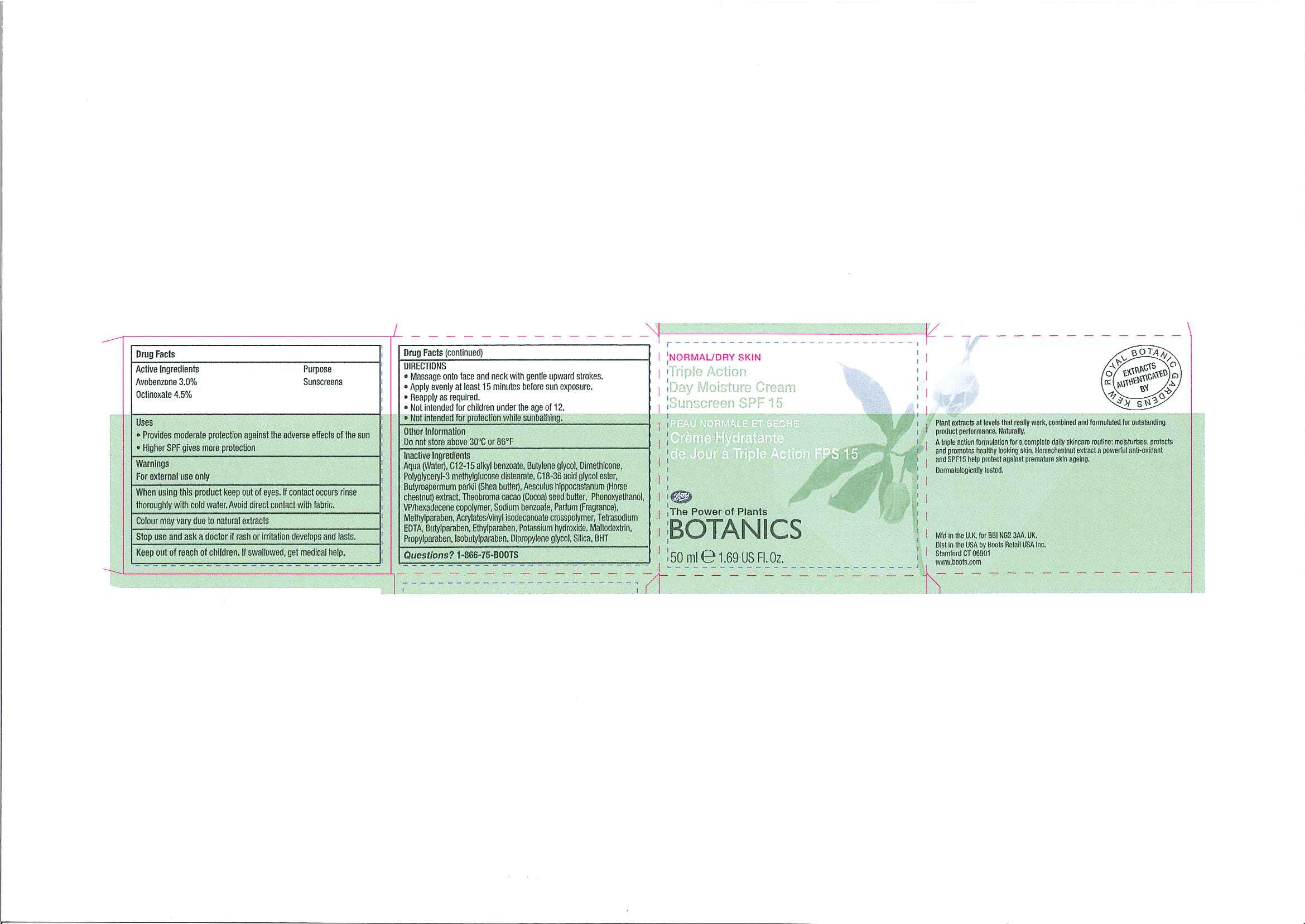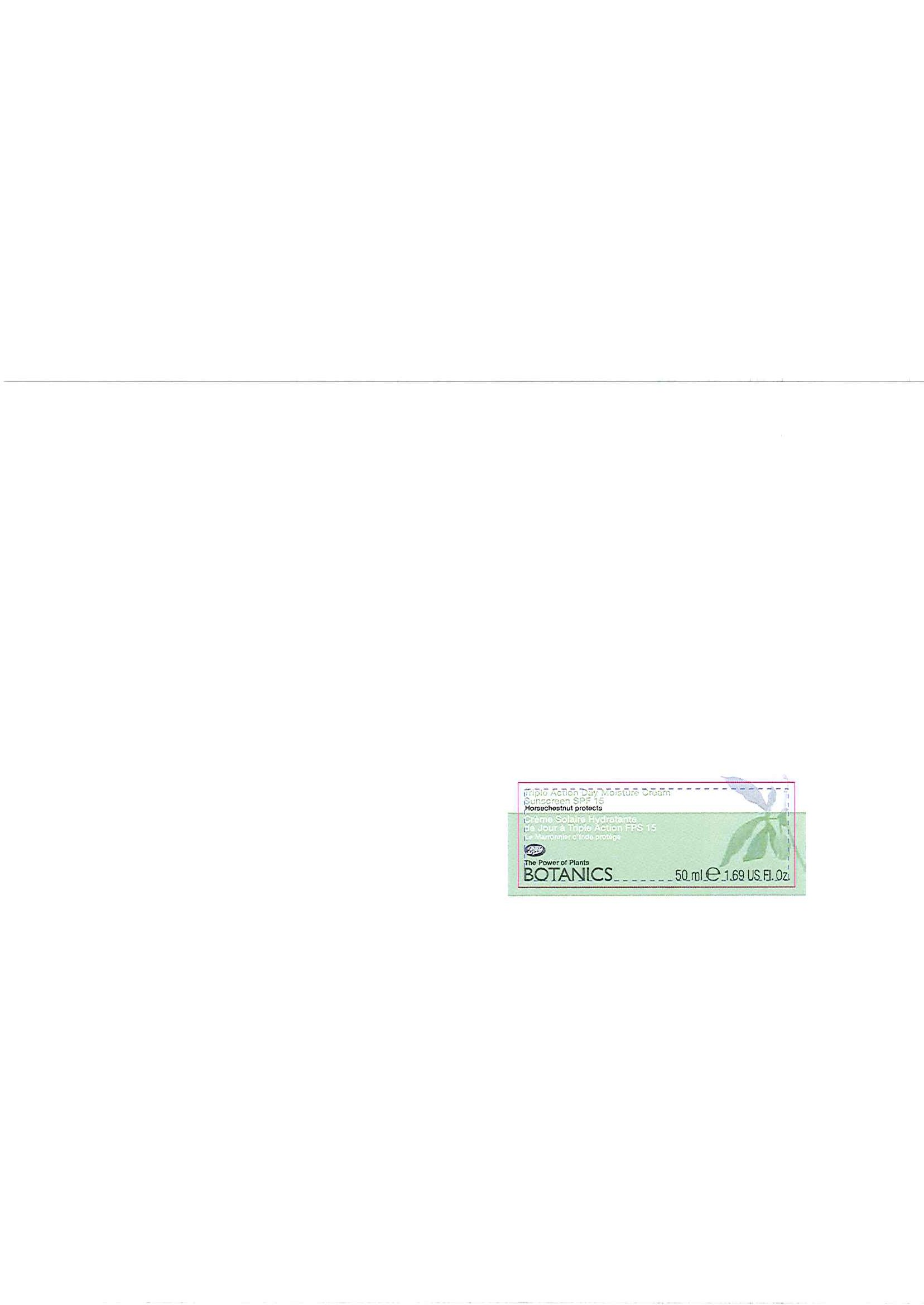 DRUG LABEL: BOTANICS TRIPLE ACTION DAY MOISTURE SUNSCREEN SPF 15
NDC: 11489-066 | Form: CREAM
Manufacturer: BCM Ltd
Category: otc | Type: HUMAN OTC DRUG LABEL
Date: 20101207

ACTIVE INGREDIENTS: OCTINOXATE 2.25 mL/50 mL; AVOBENZONE 1.5 mL/50 mL
INACTIVE INGREDIENTS: WATER; BUTYLENE GLYCOL; DIMETHICONE; SHEA BUTTER; PHENOXYETHANOL; SODIUM BENZOATE; COCOA BUTTER; HORSE CHESTNUT; METHYLPARABEN; BUTYLPARABEN; ETHYLPARABEN; POTASSIUM HYDROXIDE; MALTODEXTRIN; PROPYLPARABEN; SILICON DIOXIDE; BUTYLATED HYDROXYTOLUENE

Carton and jar labelling

ACTIVE INGREDIENT

BOTANICS TRIPLE ACTION DAY MOISTURE CREAM SUNSCREEN SPF 15

Active Ingredients Purpose

Avobenzone 3.0% Sunscreens

Octinoxate 4.5%

Uses

- Provides moderate protection against the adverse effects of the sun
- Higher SPF gives more protection

Warnings

For external use only

When using this product keep out of eyes. If contact occurs rinse thoroughly with cold water. Avoid direct contact with fabric.

HOW SUPPLIED

Colour may vary due to natural extracts

Stop use and ask a doctor if rash or irritation develops and lasts.

Keep out of reach of children. If swallowed, get medical help.

DIRECTIONS

- Massage onto face and neck with gentle upward strokes.
- Apply evenly at least 15 minutes before sun exposure.
- Reapply as required.
- Not intended for children under the age of 12.
- Not intended for protection while sunbathing.

Other Information

Do not store above 30^0C or 86^0F

Inactive Ingredients

Aqua (Water), C12-15 alkyl benzoate, Butylene glycol, Dimethicone, Polyglyceryl-3 methylglucose distearate, C18-36 acid glycol ester, Butyrospermum parkii (Shea butter), Aesculus hippocastanum (Horsechestnut) extract, Theobroma cacao (Cocoa) seed butter, Phenoxyethanol, VP/hexadecene copolymer, Sodium benzoate, Parfum (Fragrance), Methylparaben, Acrylates/vinyl isodecanoate crosspolymer, Tetrasodium EDTA, Butylparaben, Ethylparaben, Potassium hydroxide, Maltodextrin, Propylparaben, Isobutylparaben, Dipropylene glycol, Silica, BHT

Questions? 1-866-75-BOOTS

DESCRIPTION

Plant extracts at levels that really work, combined and formulated for outstanding product performance. Naturally.

A triple action formulation for a complete daily skincare routine: moisturises, protects and promotes healthy looking skin. Horsechestnut extract a powerful anti-oxidant and SPF15 help protect against premature skin ageing.

Dermatologically tested.

PATIENT COUNSELING INFORMATION

Mfd in the U.K. for BBI NG2 3AA. UK.

Dist in the USA by Boots Retail USA Inc.

Stamford CT 06901

www.boots.com

Carton label

Normal/Dry Skin

Triple Action Day Moisture Cream Sunscreen SPF 15

PEAU NORMALE ET SECHE

Crème Hydratante de Jour ā Triple Action FPS 15

Boots

The Power of Plants

BOTANICS

50ml e 1.69 US Fl. Oz

TA Day Moisture Cream carton.jpg

Jar front label

Triple Action Day Moisture Cream Sunscreen SPF 15

Horsechestnut protects

Crème Solaire Hydratante de Jour ā Triple Action FPS 15

Le Marronnier d'Inde protège

Boots

The Power of Plants

BOTANICS

50ml e 1.69 US Fl. Oz

TA Day Moisture Cream front label.jpg

Jar back label

Dermatologically tested

WARNINGS: Avoid getting directly in eyes. If contact occurs rinse thoroughly with cold water. Avoid direct contact with fabric. Colour may vary due to natural extracts.

Dermo-teste

MISE EN GARDE: Éviter tout contact avec les yeux. En cas de projection, rincer immédiatement ā l'eau froide. Éviter tout contact direct avec du tissu. La couleur peut varier en raison des extraits naturels.

ACTIVE INGREDIENTS/ACTIFS: Avobenzone 3.0% Octinoxate 4.5%

Mdf in the U.K. for/Fabriqué au R.-U. pour BBI NG2 3AA. UK.

Dist in the USA by/aux É.-U. par Boots Retail USA Inc. Stamford CT 06901

USA/Canada: Questions? 1-866-75-BOOTS

www.boots.com

TA Day Moisture Cream back label.jpg